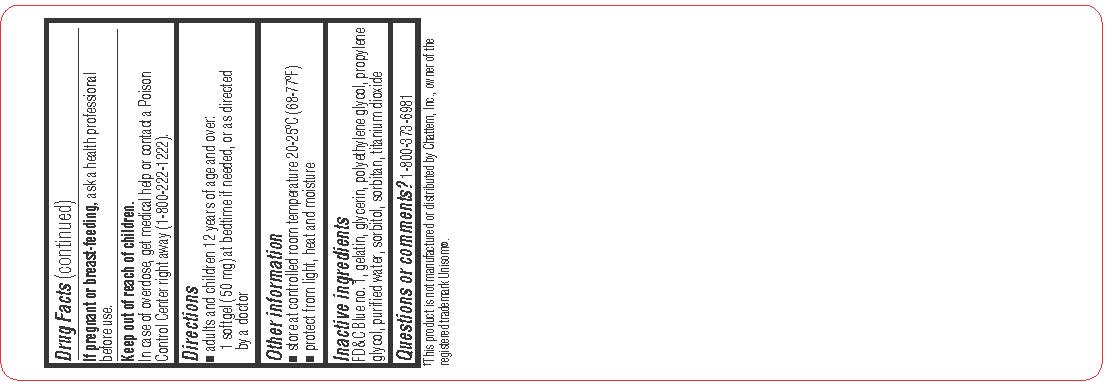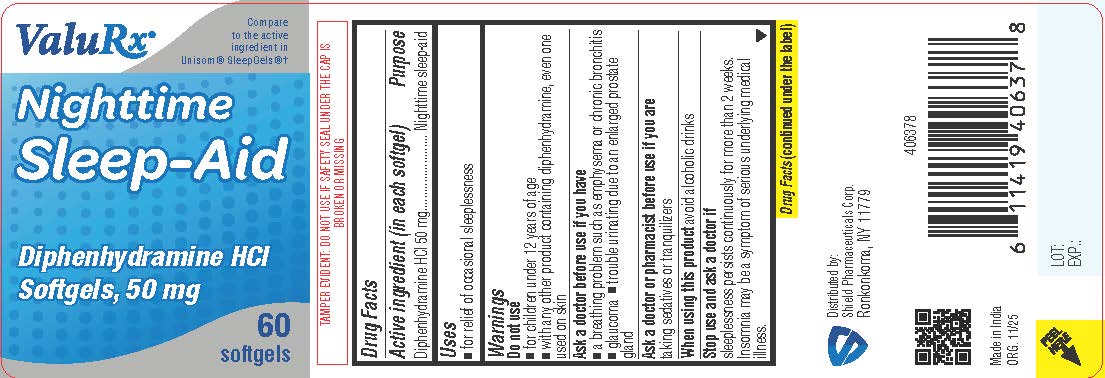 DRUG LABEL: Nighttime Sleep Aid
NDC: 83059-0122 | Form: CAPSULE, LIQUID FILLED
Manufacturer: Shield Pharmaceuticals Corp
Category: otc | Type: HUMAN OTC DRUG LABEL
Date: 20251205

ACTIVE INGREDIENTS: DIPHENHYDRAMINE HYDROCHLORIDE 50 mg/1 1
INACTIVE INGREDIENTS: FD&C BLUE NO. 1; GELATIN; GLYCERIN; POLYETHYLENE GLYCOL 400; PROPYLENE GLYCOL; SORBITOL; SORBITAN; TITANIUM DIOXIDE

Nighttime Sleep Aid

Drug Facts

Active ingredient (in each softgel)

Diphenhydramine HCl 50 mg

Purpose

Nighttime sleep-aid

Uses

• for relief of occasional sleeplessness

Do not use

• for children under 12 years of age
• with any other product containing diphenhydramine, even one used on skin

Ask a doctor before use if you have

• a breathing problem such as emphysema or chronic bronchitis
• glaucoma
• trouble urinating due to an
• enlarged prostate gland

Ask a doctor or pharmacist before useif you are taking sedatives or tranquilizers

When using this product avoid alcoholic drinks

Stop use and ask a doctor if
sleeplessness persist continuously for more than 2 weeks. Insomnia may be a symptom of serious underlying medical illness.

PREGNANCY OR BREAST FEEDING

If pregnant or breast-feeding,ask a health professional before use.

Keep out of reach of children. In case of overdose, get medical help or contact a Poison Control Center (1-800-222-1222) right away.

Directions

• adults and children 12 years of age and over: 1 softgel (50 mg) at bedtime if needed, or as directed by a doctor

Other information

• store at controlled room temperature 20-25ºC (68-77ºF)
• protect from light, heat and moisture

Inactive ingredients

FD&C Blue #1, gelatin, glycerin, polyethylene glycol, propylene glycol, purified water, sorbitol sorbitan, titanium dioxide

Questions or comments?

1-800-373-6981

Distributed by:
Shield Pharmaceuticals Corp.
Ronkonkoma, NY 11779

PRINCIPAL DISPLAY PANEL

Compare to the active ingredient in Unisom® SleepGels

Sleep-Aid

Diphenhydramine HCI Softgels, 50 mg

Label